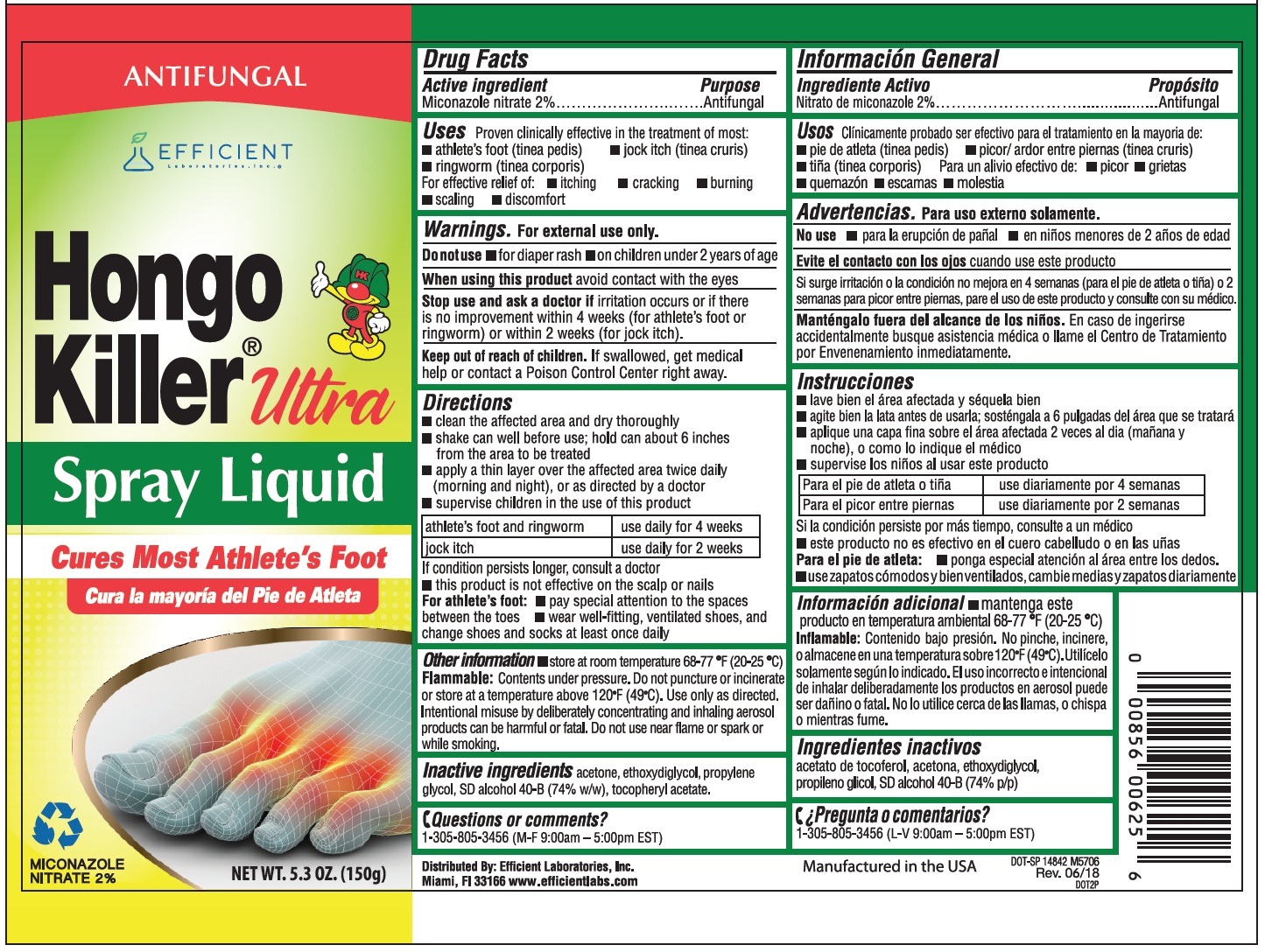 DRUG LABEL: Hongo Killer
NDC: 58593-625 | Form: AEROSOL, SPRAY
Manufacturer: Efficient Laboratories Inc
Category: otc | Type: HUMAN OTC DRUG LABEL
Date: 20251014

ACTIVE INGREDIENTS: MICONAZOLE NITRATE 0.2 g/10 g
INACTIVE INGREDIENTS: ACETONE; DIETHYLENE GLYCOL MONOETHYL ETHER; PROPYLENE GLYCOL; ALCOHOL; .ALPHA.-TOCOPHEROL ACETATE

Drug Facts

Active Ingredients: Purpose

Miconazole Nitrate 2%..... Antifungal

Purpose

Antifungal

Warnings

For external use only

Flammable:Contents under pressure. Do not puncture or incinerate or store at a temperature above 120 degrees F. Use only as directed. intentional misuse by deliberately concentrating and inhaling aerosol products can be harmful or fatal. Do not use near flame or spark or while smoking.

Do not use

- for diaper rash
- on chuldren under 2 years of age

When using this product avoid contact with the eyes

S top use and ask a doctor if irritation occurs or if there is no improvement within 4 weeks (for athlete's foot or ringworm) or within 2 weeks (for jock itch).

Keep out of reach of children. If swallowed, get medical help or contact a Poison Control Center right away.

Directions

- clean the affected area and dry thoroughly
- shake can well before use: Hold can about 6 inches from the area to be treated.
- apply a thin layer over the affected area twice daily (morning and night), or as directed by a doctor
- supervise children in the use of this product

Athlete's Foot and Ringworm - use daily for 4 weeks
Jock Itch - use daily for 2 weeks

If condition persists longer, consult a doctor
This product is not effective on the scalp or nails For athlete's foot:

- pay special attention to the spaces between the toes
- wear well-fitting, ventilated shoes, and change shoes and socks at least once daily

Uses

Proven clinically effective in the treatment of most:

- athlete's foot (tinea pedis)
- jock itch (tinea cruris)
- ringworm (tinea corporis)

For effective relief of:

- itching
- cracking
- burning
- scaling
- discomfort

Questions or comments?

Please Call 305-805-3456 (M-F 9:00-5:00 pm EST)

INACTIVE INGREDIENT

Inactive ingredients acetone, ethoxydiglycol, propylene glycol, SD alcohol 40-B (74% w/w), tocopheryl acetate